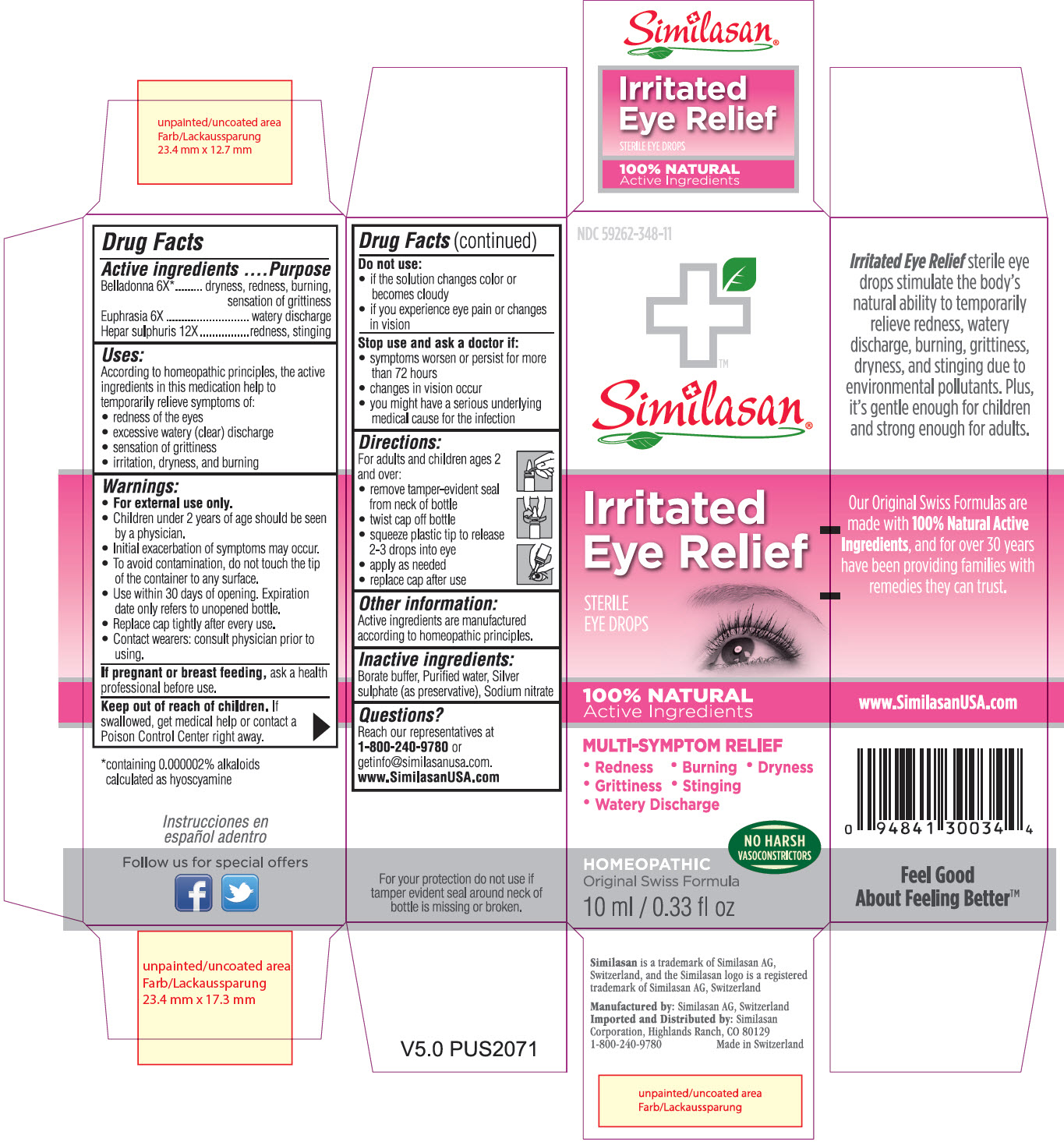 DRUG LABEL: Irritated Eye Relief
NDC: 59262-348 | Form: SOLUTION/ DROPS
Manufacturer: Similasan Corporation
Category: homeopathic | Type: HUMAN OTC DRUG LABEL
Date: 20130719

ACTIVE INGREDIENTS: ATROPA BELLADONNA 6 [hp_X]/10 mL; EUPHRASIA STRICTA 6 [hp_X]/10 mL; CALCIUM SULFIDE 12 [hp_X]/10 mL
INACTIVE INGREDIENTS: BORIC ACID; WATER; SILVER SULFATE; SODIUM NITRATE

Irritated Eye Relief

Active Ingredient

Belladonna 6X*
*containing 0.000002% alkaloids calculated as hyoscyamine

Purpose

dryness, redness, burning, sensation of grittiness

Active Ingredient

Euphrasia 6X

Purpose

watery discharge

Active Ingredient

Hepar sulphuris 12X

Purpose

redness, stinging

Uses:

According to homeopathic principles, the active ingredients in this medication help to temporarily relieve symptoms of:

- redness of the eyes
- excessive watery (clear) discharge
- sensation of grittiness
- irritation, dryness, and burning

Warnings:

- For external use only.
- Children under 2 years of age should be seen by a physician.
- Initial exacerbation of symptoms may occur.
- To avoid contamination, do not touch the tip of the container to any surface.
- Use within 30 days of opening. Expiration date only refers to unopened bottle.
- Replace cap tightly after every use.
- Contact wearers: consult a physician prior to using.

If pregnant or breast feeding,

ask a health professional before use.

Keep out of reach of children.

If swallowed, get medical help or contact a Poison Control Center right away.

Do not use:

- if the solution changes color or becomes cloudy
- if you experience eye pain or changes in vision

Stop use and ask a doctor if:

- symptoms worsen or persist for more than 72 hours
- changes in vision occur
- you might have a serious underlying medical cause for the infection

Directions:

For adults and children ages 2 and over:

- remove tamper-evident seal from neck of bottle
- twist cap off bottle
- squeeze plastic tip to release 2-3 drops into eye
- apply as needed
- replace cap after use

Other Information:

Active ingredients are manufactured according to homeopathic principles.

Inactive ingredients:

Borate buffer, Purified water, Silver sulphate (as preservative), Sodium nitrate

Questions?

Reach our representatives at 1-800-240-9780 or getinfo@similasanusa.com.
www.SimilasanUSA.com

Prinicipal Display Panel

NDC 59262-348-11
Similasan
Irritated Eye Relief
STERILE EYE DROPS
10 ml / 0.33 fl oz